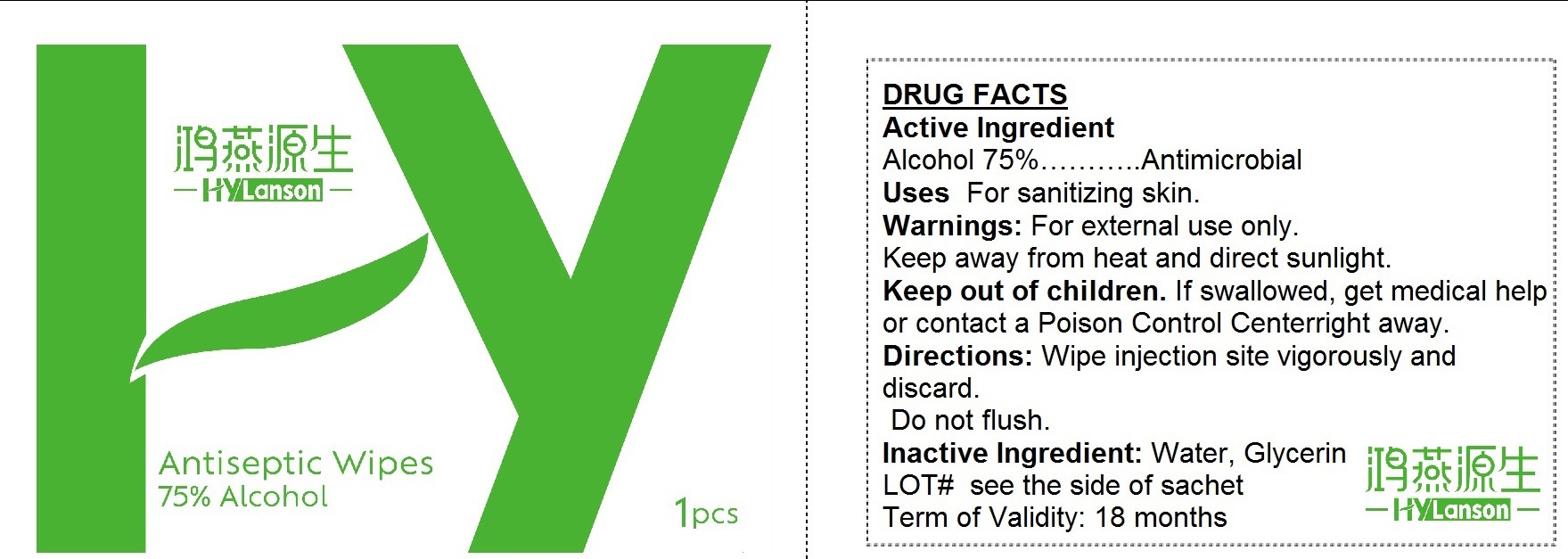 DRUG LABEL: HyLanson Antiseptic Wipes 75 Alcohol 60mmX80mm
NDC: 77678-002 | Form: CLOTH
Manufacturer: Hebei Zihan Textile Co., Ltd
Category: otc | Type: HUMAN OTC DRUG LABEL
Date: 20241219

ACTIVE INGREDIENTS: ALCOHOL 0.75 mL/1 mL
INACTIVE INGREDIENTS: WATER; GLYCERIN

HyLanson Antiseptic Wipes 75% Alcohol 60mmx80mm

Active Ingredient

Alcohol 75%

PURPOSE

Antimicrobial

Uses

For sanitizing skin.

Warnings:

For external use only.

Keep away from heat and direct sunlight.

Keep out of children.

If swallowed, get medical help or contact a Poison Control Centerright away.

Directions:

Wipe injection site vigorously and discard. Do not flush.

Inactive Ingredient:

Water, Glycerin LOT# see the side of sachet Term of Validity: 18 months